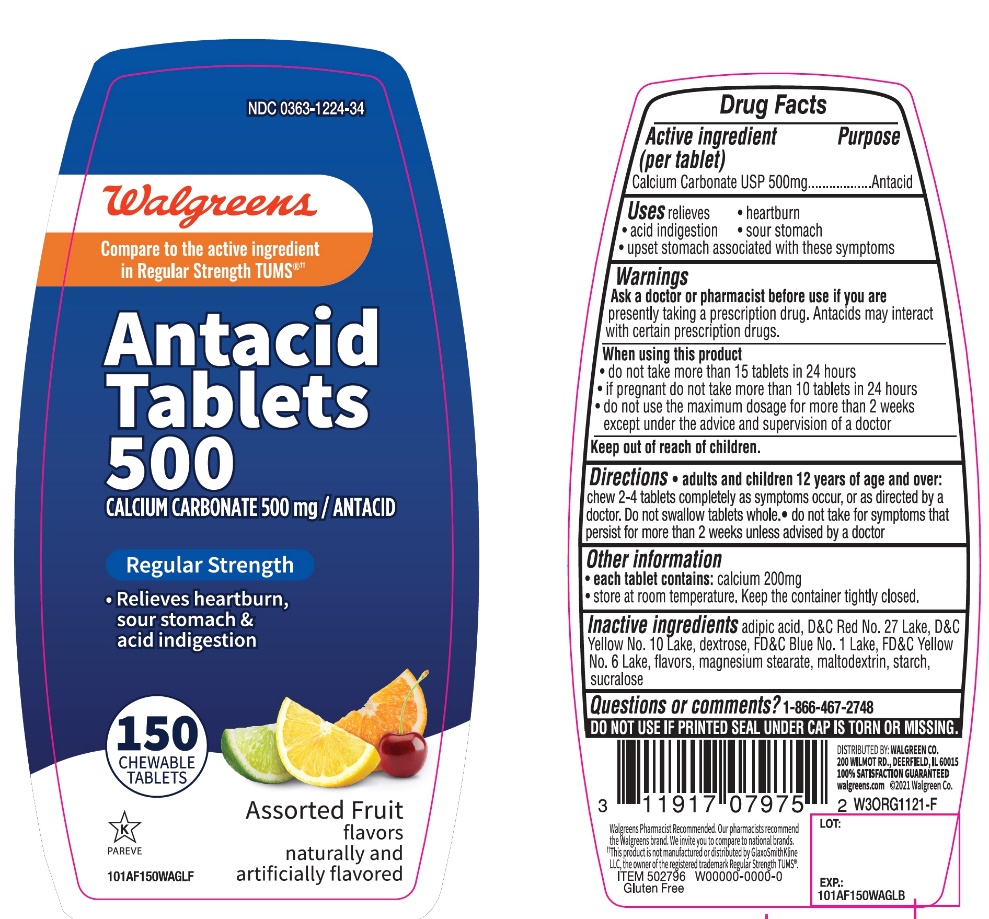 DRUG LABEL: Antacid Regular strength
NDC: 0363-1224 | Form: TABLET, CHEWABLE
Manufacturer: WALGREEN CO.
Category: otc | Type: HUMAN OTC DRUG LABEL
Date: 20251217

ACTIVE INGREDIENTS: CALCIUM CARBONATE 500 mg/1 1
INACTIVE INGREDIENTS: ADIPIC ACID; D&C RED NO. 27; D&C YELLOW NO. 10; DEXTROSE, UNSPECIFIED FORM; FD&C BLUE NO. 1; FD&C YELLOW NO. 6; MAGNESIUM STEARATE; MALTODEXTRIN; STARCH, CORN; SUCRALOSE

Walgreens Regular Strength Assorted Fruits Chewable Tablets

Active ingredient (per tablet)

Calcium Carbonate USP 500 mg

Purpose

Antacid

Uses

relieves

• heartburn

• acid indigestion

• sour stomach

• upset stomach associated with these symptoms

Warnings

Ask a doctor or pharmacist before use if you arepresently taking a prescription drug. Antacids may interact with certain prescription drugs.

When using this product

- do not take more than 15 tablets in 24 hours
- If pregnant do not take more than10 tablets in 24 hours
- do not use the maximum dosage for more than 2 weeks except under the advice and supervision of a doctor.

Directions

- adults and children 12 years and over: chew 2-4 tablets completely as symptoms occur, or as directed by a doctor. Do not swallow tablets whole.
- do not take for symptoms that persist for more than 2 weeks unless advised by a doctor.

Other information

• each tablet contains:elemental calcium 200 mg

• store at room temperature. Keep the container tightly closed

Inactive ingredients

adipic acid, D&C Red No. 27, D&C yellow No. 10, dextrose, FD&C Blue No. 1, FD & C Yellow No. 6, flavors, magnesium stearate, maltodextrin, starch, sucralose

Questions or comments?

1-866-467-2748

SAFETY SEALED: DO NOT USE IF PRINTED SEAL UNDER CAP IS TORN OR MISSING

Package/Label Principal Display Panel

Walgreens

Compare to Tum®active ingredient††

Antacid Tablets 500

Calcium Carbonate 500 mg/Antacid

REGULAR STRENGTH

- Relieves heartburn, sour stomach & acid indigestion

ASSORTED FRUIT FLAVORS

GLUTEN-FREE

Walgreens Pharmacist Recommended

Walgreens Pharmacist Survey

DISTRIBUTED BY: WALGREEN CO.

200 WILMOT RD.,DEERFIELD,IL 60015

100% SATISFACTION GUARANTEED

Walgreens.com ©2017 Walgreen Co.

MADE IN U.S.A

††This product is not manufactured or distributed by GlaxoSmithKline, the distributor of TUMS®.

Package Label Display for 150 Chewable Tablets